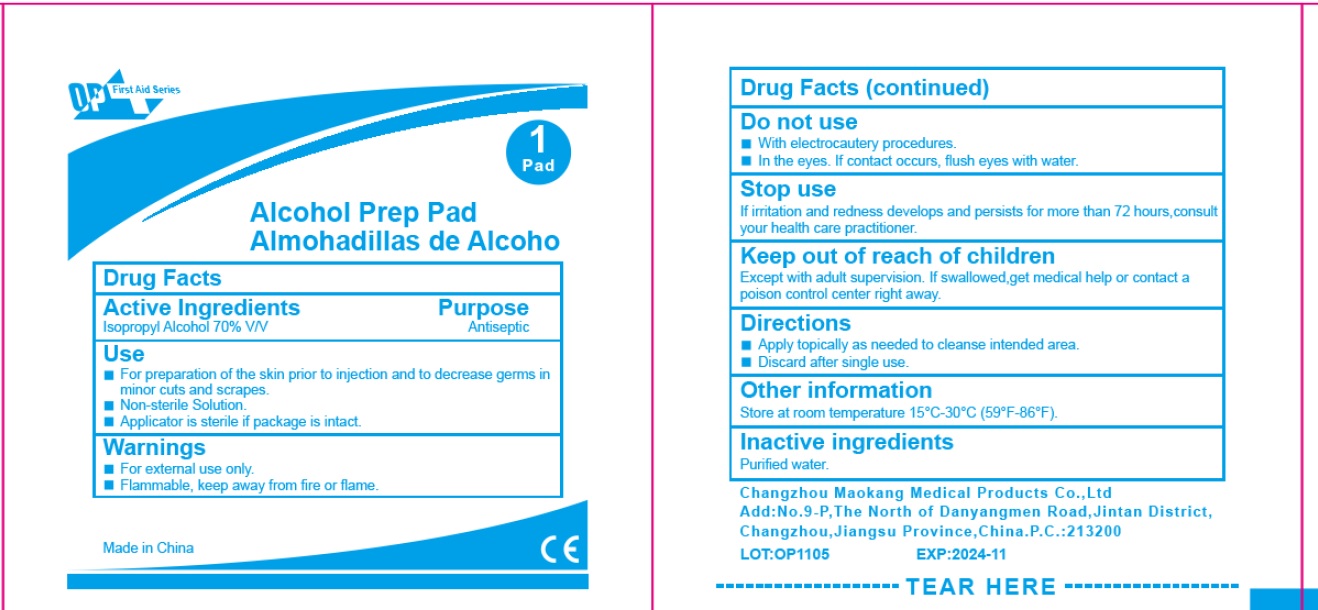 DRUG LABEL: OP First Aid Series Alcohol Prep Pad
NDC: 72459-010 | Form: CLOTH
Manufacturer: Yiwu Ori-Power Medtech Co., Ltd.
Category: otc | Type: HUMAN OTC DRUG LABEL
Date: 20260101

ACTIVE INGREDIENTS: ISOPROPYL ALCOHOL 0.7 mL/1 mL
INACTIVE INGREDIENTS: WATER

OP First Aid Series Alcohol Prep Pad

Active Ingredients

Isopropyl Alcohol 70% V/V

Purpose

Antiseptic

Use

- For Preparation of the skin prior to injection and to decrease germs in minor cuts and scrapes.
- Non-sterile Solution.
- Applicator is sterile if package is intact.

Warnings

- For external use only.
- Flammable, keep away from fire or flame.

Do not use

- With electrocautery procedures.
- In the eyes. If contact occurs, flush eyes with water.

Stop use

If irritation and redness develops and persists for more than 72 hours, consult your health care practitioner.

Keep out of reach of children

Except with adult supervision. If swallowed, get medical help or contact a poison control center right away.

Directions

- Apply topically as needed to cleanse intended area.
- Discard after single use.

Other information

Store at room temperature 15°C-30°C (59°F-86°F).

Inactive ingredients

Purified water.